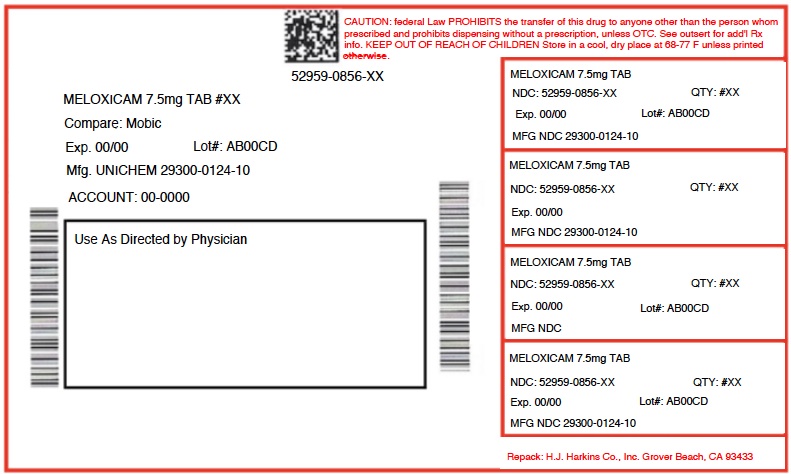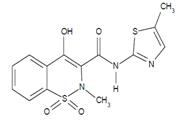 DRUG LABEL: MELOXICAM
NDC: 52959-856 | Form: TABLET
Manufacturer: H.J. Harkins Company, Inc.
Category: prescription | Type: HUMAN PRESCRIPTION DRUG LABEL
Date: 20180905

ACTIVE INGREDIENTS: MELOXICAM 7.5 mg/1 1

0856-14,15,20,21,30,36,45,60,90,01

WARNING: RISK OF SERIOUS CARDIOVASCULAR AND GASTROINTESTINAL EVENTS

Cardiovascular Thrombotic Events

Nonsteroidal anti-inflammatory drugs (NSAIDs) cause an increased risk of serious cardiovascular thrombotic events, including myocardial infarction and stroke, which can be fatal. This risk may occur early in treatment and may increase with duration of use [see Warnings and Precautions (5.1) ].
Meloxicam tablets are contraindicated in the setting of coronary artery bypass graft (CABG) surgery [see Contraindications (4) and Warnings and Precautions (5.1) ].

Gastrointestinal Bleeding, Ulceration, and Perforation

NSAIDs cause an increased risk of serious gastrointestinal (GI) adverse events including bleeding, ulceration, and perforation of the stomach or intestines, which can be fatal. These events can occur at any time during use and without warning symptoms. Elderly patients and patients with a prior history of peptic ulcer disease and/or GI bleeding are at greater risk for serious GI events [see Warnings and Precautions (5.2) ].

INDICATIONS AND USAGE

1.1 Osteoarthritis (OA)

Meloxicam tablets are indicated for relief of the signs and symptoms of osteoarthritis [see Clinical Studies (14.1)].

1.2 Rheumatoid Arthritis (RA)

Meloxicam tablets are indicated for relief of the signs and symptoms of rheumatoid arthritis [see Clinical Studies (14.1)].

1.3 Juvenile Rheumatoid Arthritis (JRA) Pauciarticular and Polyarticular Course

Meloxicam tablets are indicated for relief of the signs and symptoms of pauciarticular or polyarticular course Juvenile Rheumatoid Arthritis in patients who weigh ≥60 kg [see Dosage and Administration (2.4) and Clinical Studies (14.2)].

DOSAGE AND ADMINISTRATION

2.1 General Dosing Instructions

Carefully consider the potential benefits and risks of Meloxicam tablets and other treatment options before deciding to use Meloxicam tablets. Use the lowest effective dosage for the shortest duration consistent with individual patient treatment goals [see Warnings and Precautions (5)].

After observing the response to initial therapy with Meloxicam tablets, adjust the dose to suit an individual patient's needs.

In adults, the maximum recommended daily oral dose of Meloxicam tablets is 15 mg regardless of formulation. In patients with hemodialysis, a maximum daily dosage of 7.5 mg is recommended [see Use in Specific Populations (8.7) and Clinical Pharmacology (12.3)].

Meloxicam tablets may be taken without regard to timing of meals.

2.2 Osteoarthritis

For the relief of the signs and symptoms of osteoarthritis the recommended starting and maintenance oral dose of Meloxicam tablets is 7.5 mg once daily. Some patients may receive additional benefit by increasing the dose to 15 mg once daily.

2.3 Rheumatoid Arthritis

For the relief of the signs and symptoms of rheumatoid arthritis, the recommended starting and maintenance oral dose of Meloxicam tablets is 7.5 mg once daily. Some patients may receive additional benefit by increasing the dose to 15 mg once daily.

2.4 Juvenile Rheumatoid Arthritis (JRA) Pauciarticular and Polyarticular Course

For the treatment of juvenile rheumatoid arthritis, the recommended oral dose of Meloxicam tablets is 7.5 mg once daily in children who weigh ≥60 kg. There was no additional benefit demonstrated by increasing the dose above 7.5 mg in clinical trials.

Meloxicam tablets should not be used in children who weigh <60 kg.

2.5 Renal Impairment

The use of Meloxicam tablets in subjects with severe renal impairment is not recommended.

In patients on hemodialysis, the maximum dosage of Meloxicam tablets is 7.5 mg per day [see Clinical Pharmacology (12.3)].

2.6 Non-Interchangeability with Other Formulations of Meloxicam

Meloxicam tablets have not shown equivalent systemic exposure to other approved formulations of oral meloxicam. Therefore, Meloxicam tablets are not interchangeable with other formulations of oral meloxicam product even if the total milligram strength is the same. Do not substitute similar dose strengths of Meloxicam tablets with other formulations of oral meloxicam product.

CONTRAINDICATIONS

Meloxicam tablets are contraindicated in the following patients:

Known hypersensitivity (e.g., anaphylactic reactions and serious skin reactions) to meloxicam or any components of the drug product [see Warnings and Precautions (5.7, 5.9) ]
History of asthma, urticaria, or other allergic-type reactions after taking aspirin or other NSAIDs. Severe, sometimes fatal, anaphylactic reactions to NSAIDs have been reported in such patients [see Warnings and Precautions (5.7, 5.8) ]
In the setting of coronary artery bypass graft (CABG) surgery [see Warnings and Precautions (5.1) ]

WARNINGS AND PRECAUTIONS

5.1 Cardiovascular Thrombotic Events

Clinical trials of several COX-2 selective and nonselective NSAIDs of up to three years duration have shown an increased risk of serious cardiovascular (CV) thrombotic events, including myocardial infarction (MI) and stroke, which can be fatal. Based on available data, it is unclear that the risk for CV thrombotic events is similar for all NSAIDs. The relative increase in serious CV thrombotic events over baseline conferred by NSAID use appears to be similar in those with and without known CV disease or risk factors for CV disease. However, patients with known CV disease or risk factors had a higher absolute incidence of excess serious CV thrombotic events, due to their increased baseline rate. Some observational studies found that this increased risk of serious CV thrombotic events began as early as the first weeks of treatment. The increase in CV thrombotic risk has been observed most consistently at higher doses.

To minimize the potential risk for an adverse CV event in NSAID-treated patients, use the lowest effective dose for the shortest duration possible. Physicians and patients should remain alert for the development of such events, throughout the entire treatment course, even in the absence of previous CV symptoms. Patients should be informed about the symptoms of serious CV events and the steps to take if they occur.

There is no consistent evidence that concurrent use of aspirin mitigates the increased risk of serious CV thrombotic events associated with NSAID use. The concurrent use of aspirin and an NSAID, such as meloxicam, increases the risk of serious gastrointestinal (GI) events [see Warnings and Precautions (5.2)].

Status Post Coronary Artery Bypass Graft (CABG) Surgery

Two large, controlled clinical trials of a COX-2 selective NSAID for the treatment of pain in the first 10-14 days following CABG surgery found an increased incidence of myocardial infarction and stroke. NSAIDs are contraindicated in the setting of CABG [see Contraindications (4)].

Post-MI Patients

Observational studies conducted in the Danish National Registry have demonstrated that patients treated with NSAIDs in the post-MI period were at increased risk of reinfarction, CV-related death, and all-cause mortality beginning in the first week of treatment. In this same cohort, the incidence of death in the first year post-MI was 20 per 100 person years in NSAID-treated patients compared to 12 per 100 person years in non-NSAID exposed patients. Although the absolute rate of death declined somewhat after the first year post-MI, the increased relative risk of death in NSAID users persisted over at least the next four years of follow-up.

Avoid the use of Meloxicam in patients with a recent MI unless the benefits are expected to outweigh the risk of recurrent CV thrombotic events. If Meloxicam is used in patients with a recent MI, monitor patients for signs of cardiac ischemia.

5.2 Gastrointestinal Bleeding, Ulceration, and Perforation

NSAIDs, including meloxicam, can cause serious gastrointestinal (GI) adverse events including inflammation, bleeding, ulceration, and perforation of the esophagus, stomach, small intestine, or large intestine, which can be fatal. These serious adverse events can occur at any time, with or without warning symptoms, in patients treated with NSAIDs. Only one in five patients who develop a serious upper GI adverse event on NSAID therapy is symptomatic. Upper GI ulcers, gross bleeding, or perforation caused by NSAIDs occurred in approximately 1% of patients treated for 3-6 months, and in about 2-4% of patients treated for one year. However, even short-term NSAID therapy is not without risk.

Risk Factors for GI Bleeding, Ulceration, and Perforation

Patients with a prior history of peptic ulcer disease and/or GI bleeding who used NSAIDs had a greater than 10-fold increased risk for developing a GI bleed compared to patients without these risk factors. Other factors that increase the risk of GI bleeding in patients treated with NSAIDs include longer duration of NSAID therapy; concomitant use of oral corticosteroids, aspirin, anticoagulants, or selective serotonin reuptake inhibitors (SSRIs); smoking; use of alcohol; older age; and poor general health status. Most postmarketing reports of fatal GI events occurred in elderly or debilitated patients. Additionally, patients with advanced liver disease and/or coagulopathy are at increased risk for GI bleeding.

Strategies to Minimize the GI Risks in NSAID-treated patients:

Use the lowest effective dosage for the shortest possible duration.
Avoid administration of more than one NSAID at a time.
Avoid use in patients at higher risk unless benefits are expected to outweigh the increased risk of bleeding. For such patients, as well as those with active GI bleeding, consider alternate therapies other than NSAIDs.
Remain alert for signs and symptoms of GI ulceration and bleeding during NSAID therapy.
If a serious GI adverse event is suspected, promptly initiate evaluation and treatment, and discontinue Meloxicam until a serious GI adverse event is ruled out.
In the setting of concomitant use of low-dose aspirin for cardiac prophylaxis, monitor patients more closely for evidence of GI bleeding [see Drug Interactions (7) ].

5.3 Hepatotoxicity

Elevations of ALT or AST (three or more times the upper limit of normal [ULN]) have been reported in approximately 1% of NSAID-treated patients in clinical trials. In addition, rare, sometimes fatal, cases of severe hepatic injury, including fulminant hepatitis, liver necrosis, and hepatic failure have been reported.

Elevations of ALT or AST (less than three times ULN) may occur in up to 15% of patients treated with NSAIDs including meloxicam.

Inform patients of the warning signs and symptoms of hepatotoxicity (e.g., nausea, fatigue, lethargy, diarrhea, pruritus, jaundice, right upper quadrant tenderness, and "flu-like" symptoms). If clinical signs and symptoms consistent with liver disease develop, or if systemic manifestations occur (e.g., eosinophilia, rash, etc.), discontinue Meloxicam immediately, and perform a clinical evaluation of the patient [see Use in Specific Populations (8.6) and Clinical Pharmacology (12.3)].

5.4 Hypertension

NSAIDs, including Meloxicam, can lead to new onset or worsening of preexisting hypertension, either of which may contribute to the increased incidence of CV events. Patients taking angiotensin converting enzyme (ACE) inhibitors, thiazide diuretics, or loop diuretics may have impaired response to these therapies when taking NSAIDs [see Drug Interactions (7)].

Monitor blood pressure (BP) during the initiation of NSAID treatment and throughout the course of therapy.

5.5 Heart Failure and Edema

The Coxib and traditional NSAID Trialists' Collaboration meta analysis of randomized controlled trials demonstrated an approximately two-fold increase in hospitalizations for heart failure in COX-2 selective-treated patients and nonselective NSAID-treated patients compared to placebo-treated patients. In a Danish National Registry study of patients with heart failure, NSAID use increased the risk of MI, hospitalization for heart failure, and death.

Additionally, fluid retention and edema have been observed in some patients treated with NSAIDs. Use of meloxicam may blunt the CV effects of several therapeutic agents used to treat these medical conditions (e.g., diuretics, ACE inhibitors, or angiotensin receptor blockers [ARBs]) [see Drug Interactions (7)].

Avoid the use of Meloxicam in patients with severe heart failure unless the benefits are expected to outweigh the risk of worsening heart failure. If Meloxicam is used in patients with severe heart failure, monitor patients for signs of worsening heart failure.

5.6 Renal Toxicity and Hyperkalemia

Renal Toxicity

Long-term administration of NSAIDs, including Meloxicam, has resulted in renal papillary necrosis, renal insufficiency, acute renal failure, and other renal injury.

Renal toxicity has also been seen in patients in whom renal prostaglandins have a compensatory role in the maintenance of renal perfusion. In these patients, administration of an NSAID may cause a dose-dependent reduction in prostaglandin formation and, secondarily, in renal blood flow, which may precipitate overt renal decompensation. Patients at greatest risk of this reaction are those with impaired renal function, dehydration, hypovolemia, heart failure, liver dysfunction, those taking diuretics and ACE inhibitors or ARBs, and the elderly. Discontinuation of NSAID therapy is usually followed by recovery to the pretreatment state.

The renal effects of Meloxicam may hasten the progression of renal dysfunction in patients with preexisting renal disease. Because some Meloxicam metabolites are excreted by the kidney, monitor patients for signs of worsening renal function.

Correct volume status in dehydrated or hypovolemic patients prior to initiating Meloxicam. Monitor renal function in patients with renal or hepatic impairment, heart failure, dehydration, or hypovolemia during use of Meloxicam [see Drug Interactions (7)].

No information is available from controlled clinical studies regarding the use of Meloxicam in patients with advanced renal disease. Avoid the use of Meloxicam in patients with advanced renal disease unless the benefits are expected to outweigh the risk of worsening renal function. If Meloxicam is used in patients with advanced renal disease, monitor patients for signs of worsening renal function [see Clinical Pharmacology (12.3)].

Hyperkalemia

Increases in serum potassium concentration, including hyperkalemia, have been reported with use of NSAIDs, even in some patients without renal impairment. In patients with normal renal function, these effects have been attributed to a hyporeninemic-hypoaldosteronism state.

5.7 Anaphylactic Reactions

Meloxicam has been associated with anaphylactic reactions in patients with and without known hypersensitivity to meloxicam and in patients with aspirin-sensitive asthma [see Contraindications (4) and Warnings and Precautions (5.8)].

Seek emergency help if an anaphylactic reaction occurs.

5.8 Exacerbation of Asthma Related to Aspirin Sensitivity

A subpopulation of patients with asthma may have aspirin-sensitive asthma which may include chronic rhinosinusitis complicated by nasal polyps; severe, potentially fatal bronchospasm; and/or intolerance to aspirin and other NSAIDs. Because cross-reactivity between aspirin and other NSAIDs has been reported in such aspirin-sensitive patients, Meloxicam is contraindicated in patients with this form of aspirin sensitivity [see Contraindications (4)]. When Meloxicam is used in patients with preexisting asthma (without known aspirin sensitivity), monitor patients for changes in the signs and symptoms of asthma.

5.9 Serious Skin Reactions

NSAIDs, including meloxicam, can cause serious skin adverse reactions such as exfoliative dermatitis, Stevens-Johnson Syndrome (SJS), and toxic epidermal necrolysis (TEN), which can be fatal. These serious events may occur without warning. Inform patients about the signs and symptoms of serious skin reactions, and to discontinue the use of Meloxicam at the first appearance of skin rash or any other sign of hypersensitivity. Meloxicam is contraindicated in patients with previous serious skin reactions to NSAIDs [see Contraindications (4)].

5.10 Premature Closure of Fetal Ductus Arteriosus

Meloxicam may cause premature closure of the fetal ductus arteriosus. Avoid use of NSAIDs, including Meloxicam, in pregnant women starting at 30 weeks of gestation (third trimester) [see Use in Specific Populations (8.1)].

5.11 Hematologic Toxicity

Anemia has occurred in NSAID-treated patients. This may be due to occult or gross blood loss, fluid retention, or an incompletely described effect on erythropoiesis. If a patient treated with Meloxicam has any signs or symptoms of anemia, monitor hemoglobin or hematocrit.

NSAIDs, including Meloxicam, may increase the risk of bleeding events. Co-morbid conditions such as coagulation disorders or concomitant use of warfarin, other anticoagulants, antiplatelet agents (e.g., aspirin), serotonin reuptake inhibitors (SSRIs) and serotonin norepinephrine reuptake inhibitors (SNRIs) may increase this risk. Monitor these patients for signs of bleeding [see Drug Interactions (7)].

5.12 Masking of Inflammation and Fever

The pharmacological activity of Meloxicam in reducing inflammation, and possibly fever, may diminish the utility of diagnostic signs in detecting infections.

5.13 Laboratory Monitoring

Because serious GI bleeding, hepatotoxicity, and renal injury can occur without warning symptoms or signs, consider monitoring patients on long-term NSAID treatment with a CBC and a chemistry profile periodically [see Warnings and Precautions (5.2, 5.3, 5.6)].

USE IN SPECIFIC POPULATIONS

8.1 Pregnancy

Risk Summary

Use of NSAIDs, including Meloxicam, during the third trimester of pregnancy increases the risk of premature closure of the fetal ductus arteriosus. Avoid use of NSAIDs, including Meloxicam, in pregnant women starting at 30 weeks of gestation (third trimester) [see Warnings and Precautions (5.10)].

There are no adequate and well-controlled studies of Meloxicam in pregnant women. Data from observational studies regarding potential embryofetal risks of NSAID use in women in the first or second trimesters of pregnancy are inconclusive. In the general U.S. population, all clinically recognized pregnancies, regardless of drug exposure, have a background rate of 2-4% for major malformations, and 15-20% for pregnancy loss.

In animal reproduction studies, embryofetal death was observed in rats and rabbits treated during the period of organogenesis with meloxicam at oral doses equivalent to 0.65- and 6.5-times the maximum recommended human dose (MRHD) of Meloxicam. Increased incidence of septal heart defects were observed in rabbits treated throughout embryogenesis with meloxicam at an oral dose equivalent to 78-times the MRHD. In pre- and post-natal reproduction studies, there was an increased incidence of dystocia, delayed parturition, and decreased offspring survival at 0.08-times MRHD of meloxicam. No teratogenic effects were observed in rats and rabbits treated with meloxicam during organogenesis at an oral dose equivalent to 2.6 and 26-times the MRHD [see Data].

Based on animal data, prostaglandins have been shown to have an important role in endometrial vascular permeability, blastocyst implantation, and decidualization. In animal studies, administration of prostaglandin synthesis inhibitors, such as meloxicam, resulted in increased pre- and post-implantation loss.

Clinical Considerations

Labor or Delivery

There are no studies on the effects of Meloxicam during labor or delivery. In animal studies, NSAIDs, including meloxicam, inhibit prostaglandin synthesis, cause delayed parturition, and increase the incidence of stillbirth.

Data

Animal Data

Meloxicam was not teratogenic when administered to pregnant rats during fetal organogenesis at oral doses up to 4 mg/kg/day (2.6-fold greater than the MRHD of 15 mg of Meloxicam based on BSA comparison). Administration of meloxicam to pregnant rabbits throughout embryogenesis produced an increased incidence of septal defects of the heart at an oral dose of 60 mg/kg/day (78-fold greater than the MRHD based on BSA comparison). The no effect level was 20 mg/kg/day (26-fold greater than the MRHD based on BSA conversion). In rats and rabbits, embryolethality occurred at oral meloxicam doses of 1 mg/kg/day and 5 mg/kg/day, respectively (0.65and 6.5-fold greater, respectively, than the MRHD based on BSA comparison) when administered throughout organogenesis.

Oral administration of meloxicam to pregnant rats during late gestation through lactation increased the incidence of dystocia, delayed parturition, and decreased offspring survival at meloxicam doses of 0.125 mg/kg/day or greater (0.08-times MRHD based on BSA comparison).

8.2 Lactation

Risk Summary

There are no human data available on whether meloxicam is present in human milk, or on the effects on breastfed infants, or on milk production. The developmental and health benefits of breastfeeding should be considered along with the mother's clinical need for Meloxicam and any potential adverse effects on the breastfed infant from the Meloxicam or from the underlying maternal condition.

Data

Animal Data

Meloxicam was present in the milk of lactating rats at concentrations higher than those in plasma.

8.3 Females and Males of Reproductive Potential

Infertility

Females

Based on the mechanism of action, the use of prostaglandin-mediated NSAIDs, including Meloxicam, may delay or prevent rupture of ovarian follicles, which has been associated with reversible infertility in some women. Published animal studies have shown that administration of prostaglandin synthesis inhibitors has the potential to disrupt prostaglandin-mediated follicular rupture required for ovulation. Small studies in women treated with NSAIDs have also shown a reversible delay in ovulation. Consider withdrawal of NSAIDs, including Meloxicam, in women who have difficulties conceiving or who are undergoing investigation of infertility.

8.4 Pediatric Use

The safety and effectiveness of meloxicam in pediatric JRA patients from 2 to 17 years of age has been evaluated in three clinical trials [see Dosage and Administration (2.3), Adverse Reactions (6.1) and Clinical Studies (14.2)].

8.5 Geriatric Use

Elderly patients, compared to younger patients, are at greater risk for NSAID-associated serious cardiovascular, gastrointestinal, and/or renal adverse reactions. If the anticipated benefit for the elderly patient outweighs these potential risks, start dosing at the low end of the dosing range, and monitor patients for adverse effects [see Warnings and Precautions (5.1, 5.2, 5.3, 5.6, 5.13)].

8.6 Hepatic Impairment

No dose adjustment is necessary in patients with mild to moderate hepatic impairment. Patients with severe hepatic impairment have not been adequately studied. Since meloxicam is significantly metabolized in the liver and hepatotoxicity may occur, use meloxicam with caution in patients with hepatic impairment [see Warnings and Precautions (5.3) and Clinical Pharmacology (12.3)].

8.7 Renal Impairment

No dose adjustment is necessary in patients with mild to moderate renal impairment. Patients with severe renal impairment have not been studied. The use of Meloxicam in subjects with severe renal impairment is not recommended. In patients on hemodialysis, meloxicam should not exceed 7.5 mg per day. Meloxicam is not dialyzable [see Dosage and Administration (2.1) and Clinical Pharmacology (12.3)].

OVERDOSAGE

Symptoms following acute NSAID overdosages have been typically limited to lethargy, drowsiness, nausea, vomiting, and epigastric pain, which have been generally reversible with supportive care. Gastrointestinal bleeding has occurred. Hypertension, acute renal failure, respiratory depression, and coma have occurred, but were rare [see Warnings and Precautions (5.1, 5.2, 5.4, 5.6)].

Manage patients with symptomatic and supportive care following an NSAID overdosage. There are no specific antidotes. Consider emesis and/or activated charcoal (60 to 100 grams in adults, 1 to 2 grams per kg of body weight in pediatric patients) and/or osmotic cathartic in symptomatic patients seen within four hours of ingestion or in patients with a large overdosage (5 to 10 times the recommended dosage). Forced diuresis, alkalinization of urine, hemodialysis, or hemoperfusion may not be useful due to high protein binding.

There is limited experience with meloxicam overdosage. Cholestyramine is known to accelerate the clearance of meloxicam. Accelerated removal of meloxicam by 4 g oral doses of cholestyramine given three times a day was demonstrated in a clinical trial. Administration of cholestyramine may be useful following an overdosage.

For additional information about overdosage treatment, call a poison control center (1-800-222-1222).

DESCRIPTION

Meloxicam Tablets USP are a nonsteroidal anti-inflammatory drug (NSAID). Each tablet contains 7.5 mg or 15 mg meloxicam for oral administration. Meloxicam is chemically designated as 4-hydroxy-2-methyl-N-(5-methyl-2-thiazolyl)-2H-1,2-benzothiazine-3-carboxamide-1,1-dioxide. The molecular weight is 351.4. Its empirical formula is C14H13N3O4S2 and it has the following structural formula:

Chemical Structure

Meloxicam is a pastel yellow solid, practically insoluble in water, with higher solubility observed in strong acids and bases. It is very slightly soluble in methanol. Meloxicam has an apparent partition coefficient (log P)app = 0.1 in n-octanol/buffer pH 7.4. Meloxicam has pKa values of 1.1 and 4.2.

Meloxicam is available as a tablet for oral administration containing 7.5 mg or 15 mg meloxicam.

The inactive ingredients in Meloxicam tablets USP include colloidal silicon dioxide, crospovidone, lactose monohydrate, magnesium stearate, microcrystalline cellulose, povidone and sodium citrate dihydrate.

CLINICAL STUDIES

14.1 Osteoarthritis and Rheumatoid Arthritis

The use of Meloxicam for the treatment of the signs and symptoms of osteoarthritis of the knee and hip was evaluated in a 12-week, double-blind, controlled trial. Meloxicam (3.75 mg, 7.5 mg, and 15 mg daily) was compared to placebo. The four primary endpoints were investigator's global assessment, patient global assessment, patient pain assessment, and total WOMAC score (a self-administered questionnaire addressing pain, function, and stiffness). Patients on Meloxicam 7.5 mg daily and Meloxicam 15 mg daily showed significant improvement in each of these endpoints compared with placebo.

The use of Meloxicam for the management of signs and symptoms of osteoarthritis was evaluated in six double-blind, active-controlled trials outside the U.S. ranging from 4 weeks' to 6 months' duration. In these trials, the efficacy of Meloxicam, in doses of 7.5 mg/day and 15 mg/day, was comparable to piroxicam 20 mg/day and diclofenac SR 100 mg/day and consistent with the efficacy seen in the U.S. trial.

The use of Meloxicam for the treatment of the signs and symptoms of rheumatoid arthritis was evaluated in a 12-week, double-blind, controlled multinational trial. Meloxicam (7.5 mg, 15 mg, and 22.5 mg daily) was compared to placebo. The primary endpoint in this study was the ACR20 response rate, a composite measure of clinical, laboratory, and functional measures of RA response. Patients receiving Meloxicam 7.5 mg and 15 mg daily showed significant improvement in the primary endpoint compared with placebo. No incremental benefit was observed with the 22.5 mg dose compared to the 15 mg dose.

14.2 Juvenile Rheumatoid Arthritis (JRA) Pauciarticular and Polyarticular Course

The use of Meloxicam for the treatment of the signs and symptoms of pauciarticular or polyarticular course Juvenile Rheumatoid Arthritis in patients 2 years of age and older was evaluated in two 12-week, double-blind, parallel-arm, active-controlled trials.

Both studies included three arms: naproxen and two doses of meloxicam. In both studies, meloxicam dosing began at 0.125 mg/kg/day (7.5 mg maximum) or 0.25 mg/kg/day (15 mg maximum), and naproxen dosing began at 10 mg/kg/day. One study used these doses throughout the 12-week dosing period, while the other incorporated a titration after 4 weeks to doses of 0.25 mg/kg/day and 0.375 mg/kg/day (22.5 mg maximum) of meloxicam and 15 mg/kg/day of naproxen.

The efficacy analysis used the ACR Pediatric 30 responder definition, a composite of parent and investigator assessments, counts of active joints and joints with limited range of motion, and erythrocyte sedimentation rate. The proportion of responders were similar in all three groups in both studies, and no difference was observed between the meloxicam dose groups.

Medication Guide for Nonsteroidal Anti-inflammatory Drugs (NSAIDs)

What is the most important information I should know about medicines called Nonsteroidal Anti-inflammatory Drugs (NSAIDs)?

NSAIDs can cause serious side effects, including:
• Increased risk of a heart attack or stroke that can lead to death . This risk may happen early in treatment and may increase:
o with increasing doses of NSAIDs
o with longer use of NSAIDs
• Do not take NSAIDs right before or after a heart surgery called a "coronary artery bypass graft (CABG)."
• Avoid taking NSAIDs after a recent heart attack, unless your healthcare provider tells you to. You may have an increased risk of another heart attack if you take NSAIDs after a recent heart attack.
• Increased risk of bleeding, ulcers, and tears (perforation) of the esophagus (tube leading from the mouth to the stomach), stomach and intestines:
o anytime during use
o without warning symptoms
o that may cause death
The risk of getting an ulcer or bleeding increases with:
o past history of stomach ulcers, or stomach or intestinal bleeding with use of NSAIDs
o taking medicines called "corticosteroids", "anticoagulants", "SSRIs", or "SNRIs"
o increasing doses of NSAIDs
o longer use of NSAIDs
o smoking
o drinking alcohol
o older age
o poor health
o advanced liver disease
o bleeding problems
NSAIDs should only be used:
o exactly as prescribed
o at the lowest dose possible for your treatment
o for the shortest time needed
What are NSAIDs?
NSAIDs are used to treat pain and redness, swelling, and heat (inflammation) from medical conditions such as different types of arthritis, menstrual cramps, and other types of short-term pain.
Who should not take NSAIDs?
Do not take NSAIDs:
• if you have had an asthma attack, hives, or other allergic reaction with aspirin or any other NSAIDs.
• right before or after heart bypass surgery.
Before taking NSAIDs, tell your healthcare provider about all of your medical conditions, including if you:
• have liver or kidney problems
• have high blood pressure
• have asthma
• are pregnant or plan to become pregnant. Talk to your healthcare provider if you are considering taking NSAIDs during pregnancy. You should not take NSAIDs after 29 weeks of pregnancy.
• are breastfeeding or plan to breast feed.
Tell your healthcare provider about all of the medicines you take, including prescription or over-the-counter medicines, vitamins or herbal supplements. NSAIDs and some other medicines can interact with each other and cause serious side effects. Do not start taking any new medicine without talking to your healthcare provider first.
What are the possible side effects of NSAIDs?
NSAIDs can cause serious side effects, including:
See "What is the most important information I should know about medicines called Nonsteroidal Anti-inflammatory Drugs (NSAIDs)?"
• new or worse high blood pressure
• heart failure
• liver problems including liver failure
• kidney problems including kidney failure
• low red blood cells (anemia)
• life-threatening skin reactions
• life-threatening allergic reactions
• Other side effects of NSAIDs include: stomach pain, constipation, diarrhea, gas, heartburn, nausea, vomiting, and dizziness.
Get emergency help right away if you get any of the following symptoms:
• shortness of breath or trouble breathing
• chest pain
• weakness in one part or side of your body
• slurred speech
• swelling of the face or throat
Stop taking your NSAID and call your healthcare provider right away if you get any of the following symptoms:
• Nausea
• more tired or weaker than usual
• diarrhea
• itching
• your skin or eyes look yellow
• indigestion or stomach pain
• flu-like symptoms
• vomit blood
• there is blood in your bowel movement or it is black and sticky like tar
• unusual weight gain
• skin rash or blisters with fever
• swelling of the arms, legs, hands and feet
If you take too much of your NSAID, call your healthcare provider or get medical help right away.
These are not all the possible side effects of NSAIDs. For more information, ask your healthcare provider or pharmacist about NSAIDs.
Call your doctor for medical advice about side effects. You may report side effects to FDA at 1-800-FDA-1088.
Other information about NSAIDs:
• Aspirin is an NSAID but it does not increase the chance of a heart attack. Aspirin can cause bleeding in the brain, stomach, and intestines. Aspirin can also cause ulcers in the stomach and intestines.
• Some NSAIDs are sold in lower doses without a prescription (over-the-counter). Talk to your healthcare provider before using over-the-counter NSAIDs for more than 10 days.
General information about the safe and effective use of NSAIDs
Medicines are sometimes prescribed for purposes other than those listed in a Medication Guide. Do not use NSAIDs for a condition for which it was not prescribed. Do not give NSAIDs to other people, even if they have the same symptoms that you have. It may harm them.
If you would like more information about NSAIDs, talk with your healthcare provider. You can ask your pharmacist or healthcare provider for information about NSAIDs that is written for health professionals.